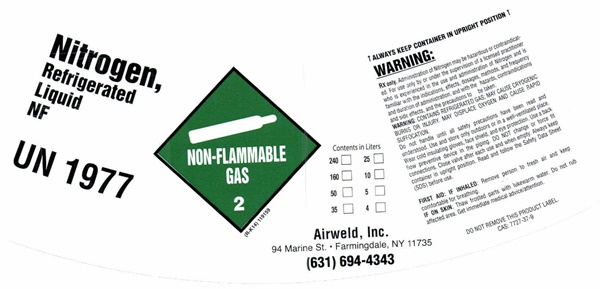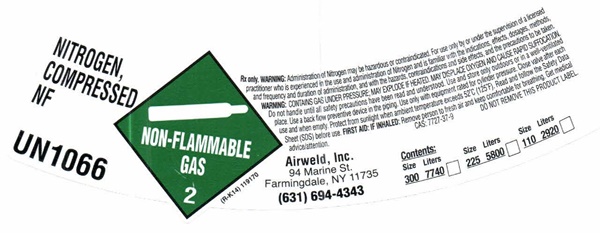 DRUG LABEL: NITROGEN
NDC: 48599-002 | Form: GAS
Manufacturer: Airweld, Inc
Category: prescription | Type: HUMAN PRESCRIPTION DRUG LABEL
Date: 20241008

ACTIVE INGREDIENTS: NITROGEN 99 L/100 L

Nitrogen - 002

Nitrogen Refrigerated Liquid NF - product label

Nitrogen Refrigerated Liquid NF

UN 1977

NON-FLAMMABLE GAS 2

(R-K14) 119159

Contents in Liters

240 25

160 10

50 5

35 4

Airweld, Inc.

94 Marine St. • Farmingdale, NY 11735

(631) 694-4343

↑ ALWAYS KEEP CONTAINER IN UPRIGHT POSITION ↑

WARNING:

RX only. Administration of Nitrogen may be hazardous or contraindicated. For use only by or under the supervision of a licensed practitioner who is experienced in the use and administration of Nitrogen and is familiar with the indications, effects, dosages, methods, and frequency and duration of administration, and with the hazards, contraindications and side effects, and the precautions to be taken.

WARNING: CONTAINS REFRIGERATED GAS; MAY CAUSE CRYOGENIC BURNS OR INJURY. MAY DISPLACE OXYGEN AND CAUSE RAPID SUFFOCATION.

Do not handle until all safety precautions have been read and understood. Use and store only outdoors or in a well-ventilated place. Wear cold insulating gloves, face shield, and eye protection. Use a back flow preventive device in the piping. DO NOT change or force fit connections. Close valve after each use and when empty. Always keep container in an upright position. Read and follow the Safety Data Sheet (SDS) before use.

FIRST AID: IF INHALED: Remove person to fresh air and keep comfortable for breathing.

IF ON SKIN: Thaw frosted parts with lukewarm water. Do not rub affected area. get immediate medical advice/attention.

DO NOT REMOVE THIS PRODUCT LABEL

CAS: 7727-37-9

NITROGEN COMPRESSED NF product label

NITROGEN COMPRESSED NF
UN 1066
NON-FLAMMABLE GAS 2

(R-K14) 119170

Rx only. WARNING: Administration of Nitrogen may be hazardous or contraindicated. For use only by or under the supervision of a licensed practitioner who is experienced in the use and administration of Nitrogen and is familiar with the indications, effects, dosages, methods, and frequency and duration of administration, and with the hazards, contraindications and side effects, and the precautions to be taken.

WARNING: CONTAINS GAS UNDER PRESSURE; MAY EXPLODE IF HEATED. MAY DISPLACE OXYGEN AND CAUSE RAPID SUFFOCATION. Do not handle until all safety precautions have been read and understood. Use and store only outdoors or in a well-ventilated place. Use a back flow preventive device in the piping. Use only with equipment rated for cylinder pressure. Close valve after each use and when empty. Protect from sunlight when ambient temperature exceeds 52°C (125°F). Read and follow the Safety Data Sheet (SDS) before use. FIRST AID: IF INHALED: Remove person to fresh air and keep comfortable for breahing. Get medical advice/attention.

CAS: 7727-37-9 DO NOT REMOVE PRODUCT LABEL

Airweld, Inc.

94 Marine St. • Farmingdale, NY 11735

(631) 694-4343

Contents:

Size Liters Size Liters Size Liters

300 7740 225 5800 110 2920